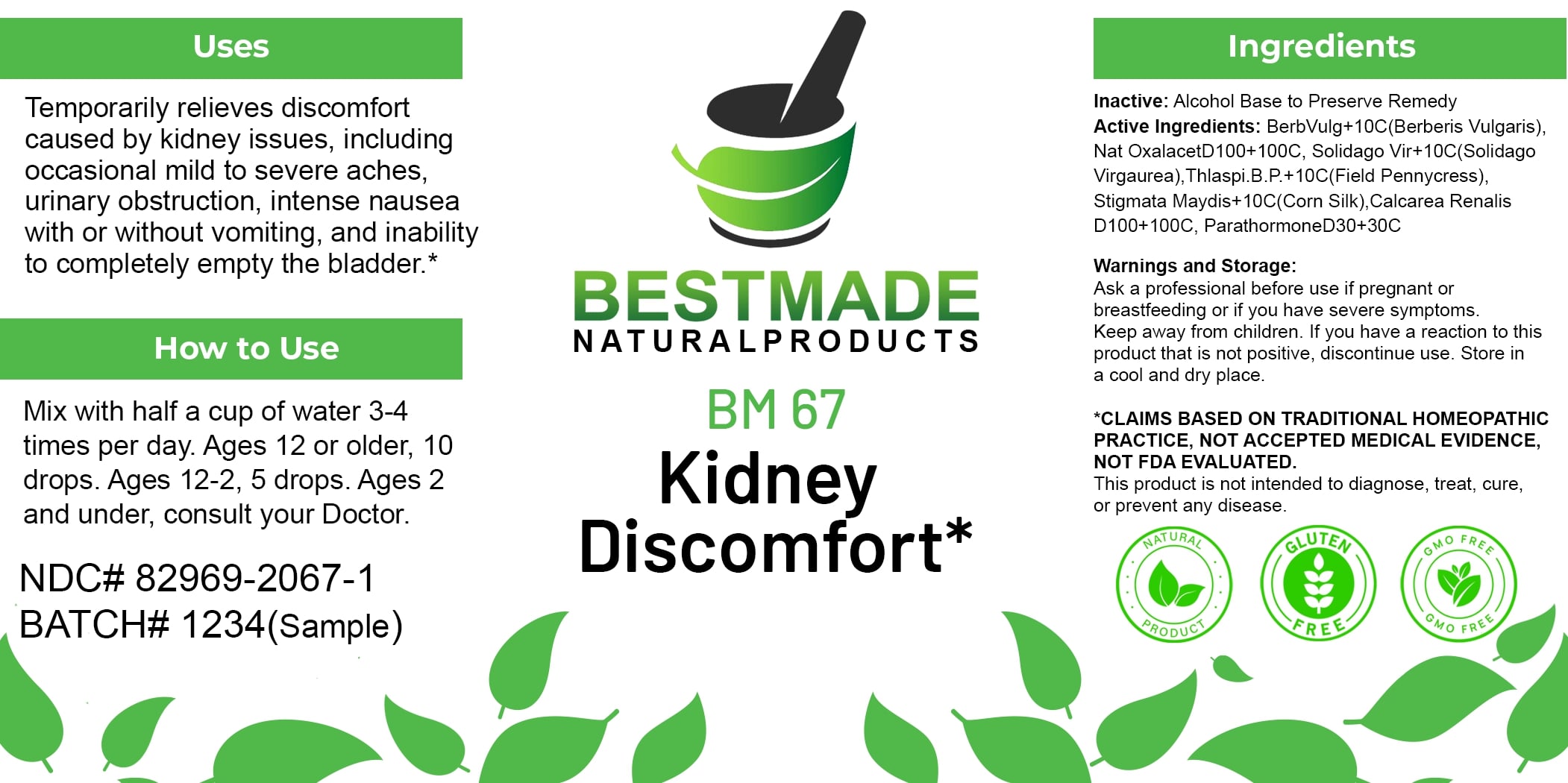 DRUG LABEL: Bestmade Natural Products BM67
NDC: 82969-2067 | Form: LIQUID
Manufacturer: Bestmade Natural Products
Category: homeopathic | Type: HUMAN OTC DRUG LABEL
Date: 20250130

ACTIVE INGREDIENTS: BERBERIS VULGARIS ROOT BARK 10 [hp_C]/100 [hp_C]; SODIUM DIETHYL OXALACETATE 100 [hp_C]/100 [hp_C]; CAPSELLA BURSA-PASTORIS 10 [hp_C]/100 [hp_C]; CALCIUM OXALATE MONOHYDRATE 100 [hp_C]/100 [hp_C]; PARATHYROID HORMONE 30 [hp_C]/100 [hp_C]; SOLIDAGO VIRGAUREA FLOWERING TOP 10 [hp_C]/100 [hp_C]; CORN SILK 10 [hp_C]/100 [hp_C]
INACTIVE INGREDIENTS: ALCOHOL 100 [hp_C]/100 [hp_C]

BM67

DOSAGE AND ADMINISTRATION

How to Use

Mix with half a cup of water 3-4 times per day. Ages 12 or older, 10 drops. Ages 12-2, 5 drops. Ages 2 and under, consult your Doctor.

INACTIVE INGREDIENT

Ingredients

Inactive: Alcohol Base to Preserve Remedy

ACTIVE INGREDIENT

Active Ingredients: BerbVulgD1+10C(Berberis Vulgaris), Nat OxalacetD100+100C, Solidago Vir+10C(Solidago Virgaurea), Thlaspi.B.P.+10C(Field Pennycress), Stigmata Maydis+10C(Corn Silk), Calcarea Renalis D100+100C, ParathormoneD30+30C

Uses

Temporarily relieves discomfort caused by kidney issues, including occasional mild to severe aches, urinary obstruction, intense nausea with or without vomiting, and inability to completely empty the bladder.*

*CLAIMS BASED ON TRADITIONAL HOMEOPATHIC PRACTICE, NOT ACCEPTED MEDICAL EVIDENCE, NOT FDA EVALUATED.

This product is not intended to diagnose, treat, cure, or prevent any disease.

Uses

Temporarily relieves discomfort caused by kidney issues, including occasional mild to severe aches, urinary obstruction, intense nausea with or without vomiting, and inability to completely empty the bladder.*

*CLAIMS BASED ON TRADITIONAL HOMEOPATHIC PRACTICE, NOT ACCEPTED MEDICAL EVIDENCE, NOT FDA EVALUATED.

This product is not intended to diagnose, treat, cure, or prevent any disease.

KEEP OUT OF REACH OF CHILDREN

Warnings and Storage:

Ask a professional before use if pregnant or breastfeeding or if you have severe symptoms. Keep away from children. If you have a reaction to this product that is not positive, discontinue use. Store in a cool and dry place.

Warnings and Storage:

Ask a professional before use if pregnant or breastfeeding or if you have severe symptoms. Keep away from children. If you have a reaction to this product that is not positive, discontinue use. Store in a cool and dry place.

*CLAIMS BASED ON TRADITIONAL HOMEOPATHIC PRACTICE, NOT ACCEPTED MEDICAL EVIDENCE, NOT FDA EVALUATED.

This product is not intended to diagnose, treat, cure, or prevent any disease.

Entire package label